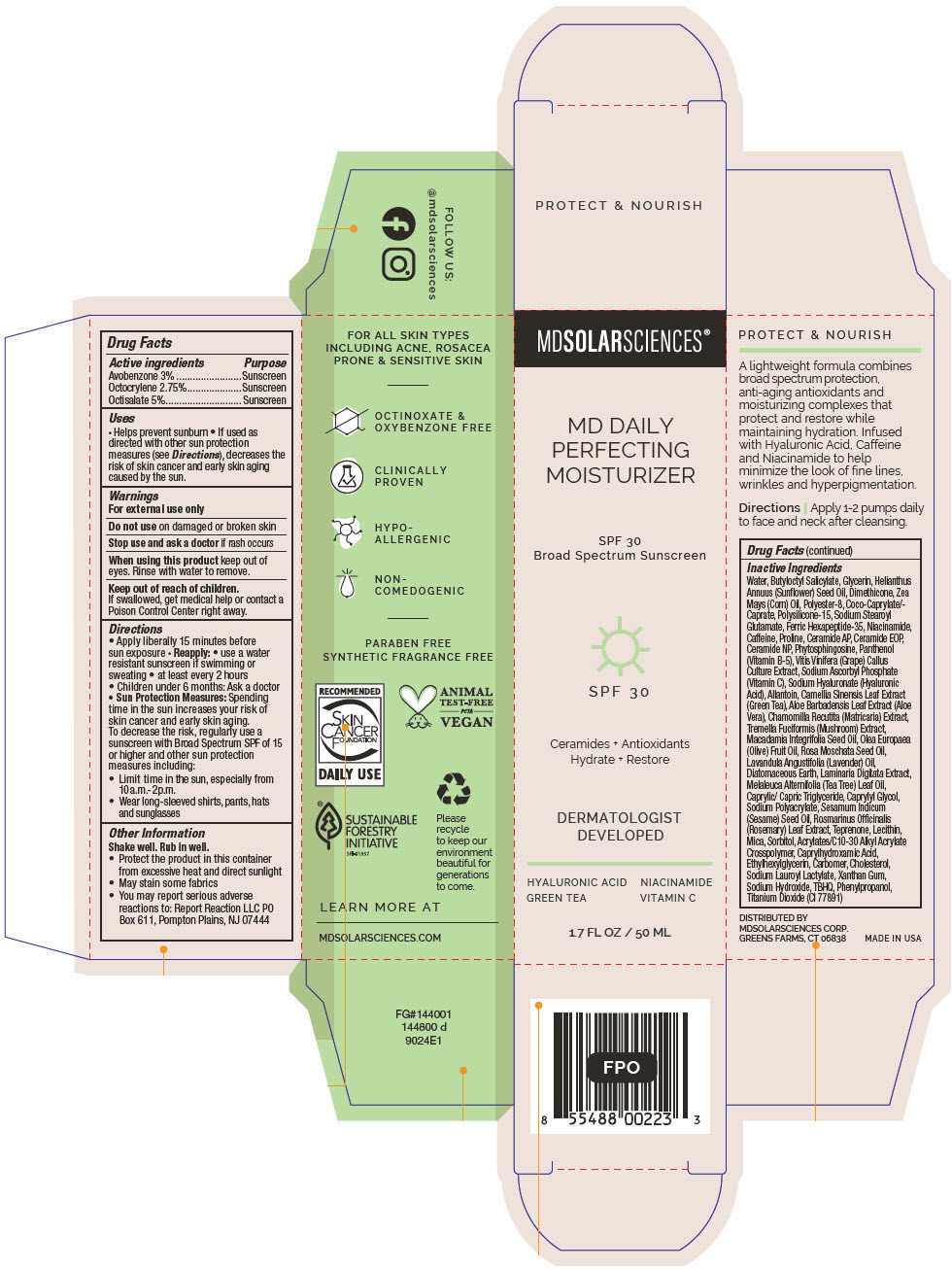 DRUG LABEL: MD Daily Perfecting Moisturizer SPF 30.
NDC: 49358-579 | Form: LOTION
Manufacturer: MDSolarSciences
Category: otc | Type: HUMAN OTC DRUG LABEL
Date: 20250605

ACTIVE INGREDIENTS: AVOBENZONE 30 mg/1 mL; OCTOCRYLENE 27.5 mg/1 mL; OCTISALATE 50 mg/1 mL
INACTIVE INGREDIENTS: WATER; BUTYLOCTYL SALICYLATE; GLYCERIN; HELIANTHUS ANNUUS FLOWERING TOP; DIMETHICONE; CORN OIL; POLYESTER-8 (1400 MW, CYANODIPHENYLPROPENOYL CAPPED); COCOYL CAPRYLOCAPRATE; POLYSILICONE-15; SODIUM STEAROYL GLUTAMATE; ACETYL HEXAPEPTIDE-8; NIACINAMIDE; CAFFEINE; PROLINE; CERAMIDE AP; CERAMIDE 9; CERAMIDE NP; PHYTOSPHINGOSINE; PANTHENOL; VITIS VINIFERA SEED; SODIUM ASCORBYL PHOSPHATE; HYALURONATE SODIUM; ALLANTOIN; GREEN TEA LEAF; ALOE VERA LEAF; CHAMOMILE; TREMELLA FUCIFORMIS FRUITING BODY; MACADAMIA OIL; OLIVE OIL; ROSA MOSCHATA SEED OIL; LAVENDER OIL; DIATOMACEOUS EARTH; LAMINARIA DIGITATA; TEA TREE OIL; MEDIUM-CHAIN TRIGLYCERIDES; CAPRYLYL GLYCOL; SODIUM POLYACRYLATE (8000 MW); SESAME OIL; ROSEMARY; TEPRENONE; HYDROGENATED SOYBEAN LECITHIN; MICA; SORBITOL; CARBOMER INTERPOLYMER TYPE A (ALLYL SUCROSE CROSSLINKED); CAPRYLHYDROXAMIC ACID; ETHYLHEXYLGLYCERIN; CARBOMER HOMOPOLYMER TYPE C (ALLYL PENTAERYTHRITOL CROSSLINKED); CHOLESTEROL; SODIUM LAUROYL LACTYLATE; XANTHAN GUM; SODIUM HYDROXIDE; TERT-BUTYLHYDROQUINONE; PHENYLPROPANOL; TITANIUM DIOXIDE

MD Daily Perfecting Moisturizer SPF 30.
SPF 30 Broad Spectrum Sunscreen UVA-UVB

Drug Facts

ACTIVE INGREDIENT

Active ingredients | Purpose
Avobenzone 3% | Sunscreen
Octocrylene 2.75% | Sunscreen
Octisalate 5% | Sunscreen

Uses

- Helps prevent sunburn
- If used as directed with other sun protection measures (see Directions), decreases the risk of skin cancer and early skin aging caused by the sun.

Warnings

For external use only

Do not useon damaged or broken skin

Stop use and ask a doctorif rash occurs

WHEN USING

When using this productkeep out of eyes. Rinse with water to remove.

Keep out of reach of children.

If swallowed, get medical help or contact a Poison Control Center right away.

Directions

- Apply liberally 15 minutes before sun exposure
- Reapply:
  - use a water resistant sunscreen if swimming or sweating
  - at least every 2 hours
- Children under 6 months: Ask a doctor
- Sun Protection Measures:Spending time in the sun increases your risk of skin cancer and early skin aging. To decrease the risk, regularly use a sunscreen with Broad Spectrum SPF of 15 or higher and other sun protection measures including:
  - Limit time in the sun, especially from 10a.m.-2p.m.
  - Wear long-sleeved shirts, pants, hats and sunglasses

Other Information

Shake well. Rub in well.

- Protect the product in this container from excessive heat and direct sunlight
- May stain some fabrics
- You may report serious adverse reactions to: Report Reaction LLC PO Box 611, Pompton Plains, NJ 07444

Inactive Ingredients

Water, Butyloctyl Salicylate, Glycerin, Helianthus Annuus (Sunflower) Seed Oil, Dimethicone, Zea Mays (Corn) Oil, Polyester-8, Coco-Caprylate/-Caprate, Polysilicone-15, Sodium Stearoyl Glutamate, Ferric Hexapeptide-35, Niacinamide, Caffeine, Proline, Ceramide AP, Ceramide EOP, Ceramide NP, Phytosphingosine, Panthenol (Vitamin B-5), Vitis Vinifera (Grape) Callus Culture Extract, Sodium Ascorbyl Phosphate (Vitamin C), Sodium Hyaluronate (Hyaluronic Acid), Allantoin, Camellia Sinensis Leaf Extract (Green Tea), Aloe Barbadensis Leaf Extract (Aloe Vera), Chamomilla Recutita (Matricaria) Extract, Tremella Fuciformis (Mushroom) Extract, Macadamia Integrifolia Seed Oil, Olea Europaea (Olive) Fruit Oil, Rosa Moschata Seed Oil, Lavandula Angustifolia (Lavender) Oil, Diatomaceous Earth, Laminaria Digitata Extract, Melaleuca Alternifolia (Tea Tree) Leaf Oil, Caprylic/ Capric Triglyceride, Caprylyl Glycol, Sodium Polyacrylate, Sesamum Indicum (Sesame) Seed Oil, Rosmarinus Officinalis (Rosemary) Leaf Extract, Teprenone, Lecithin, Mica, Sorbitol, Acrylates/C10-30 Alkyl Acrylate Crosspolymer, Caprylhydroxamic Acid, Ethylhexylglycerin, Carbomer, Cholesterol, Sodium Lauroyl Lactylate, Xanthan Gum, Sodium Hydroxide, TBHQ, Phenylpropanol, Titanium Dioxide (CI 77891)

DISTRIBUTED BY
MDSOLARSCIENCES CORP.
GREENS FARMS, CT 06838

PRINCIPAL DISPLAY PANEL - 50 ML Bottle Carton

MDSOLARSCIENCES®

MD DAILY
PERFECTING
MOISTURIZER

SPF 30
Broad Spectrum Sunscreen

SPF 30

Ceramides + Antioxidants
Hydrate + Restore

DERMATOLOGIST
DEVELOPED

HYALURONIC ACID
GREEN TEA

NIACINAMIDE
VITAMIN C

1.7 FL OZ / 50 ML